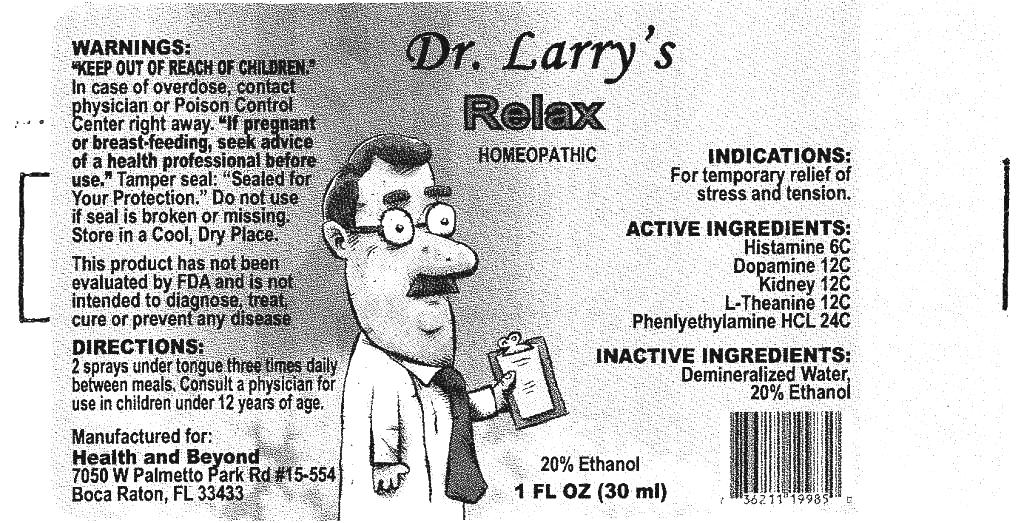 DRUG LABEL: Relax
NDC: 57520-0385 | Form: SPRAY
Manufacturer: Apotheca Company
Category: homeopathic | Type: HUMAN OTC DRUG LABEL
Date: 20110214

ACTIVE INGREDIENTS: HISTAMINE DIHYDROCHLORIDE 6 [hp_C]/1 mL; DOPAMINE 12 [hp_C]/1 mL; PORK KIDNEY 12 [hp_C]/1 mL; THEANINE 12 [hp_C]/1 mL; PHENETHYLAMINE HYDROCHLORIDE 24 [hp_C]/1 mL
INACTIVE INGREDIENTS: WATER; ALCOHOL

Relax

ACTIVE INGREDIENT

ACTIVE INGREDIENTS: Histaminum hydrochloricum 6C, Dopamine 12C, Kidney 12C, L-Theanine 12C, Phenylethylamine hydrochloricum 24C.

PURPOSE

INDICATIONS: For temporary relief of stress and tension.

WARNINGS

WARNINGS: Keep out of reach of children. In case of overdose, contact physician or Poison Control Center right away.

If pregnant or breast-feeding, seek advice of a health professional before use.

Tamper seal: "Sealed for Your Protection." Do not use if seal is broken or missing. Store in a cool, dry place.

DOSAGE AND ADMINISTRATION

DIRECTIONS: 2 sprays under tongue three times daily between meals. Consult a physician for use in children under 12 years of age.

INACTIVE INGREDIENTS: Demineralized water, 20% Ethanol.

KEEP OUT OF REACH OF CHILDREN. in case of overdose, contact physician or contact Poison Control Center right away.

INDICATIONS: For temporary relief of stress and tension.

QUESTIONS

Manufactured for:
Health and Beyond
7050 W Palmetto Park rd #15-554
Boca Raton, FL 33433

PACKAGE LABEL

Dr. Larry"s

RELAX

HOMEOPATHIC

1 FL OZ (30 ml)